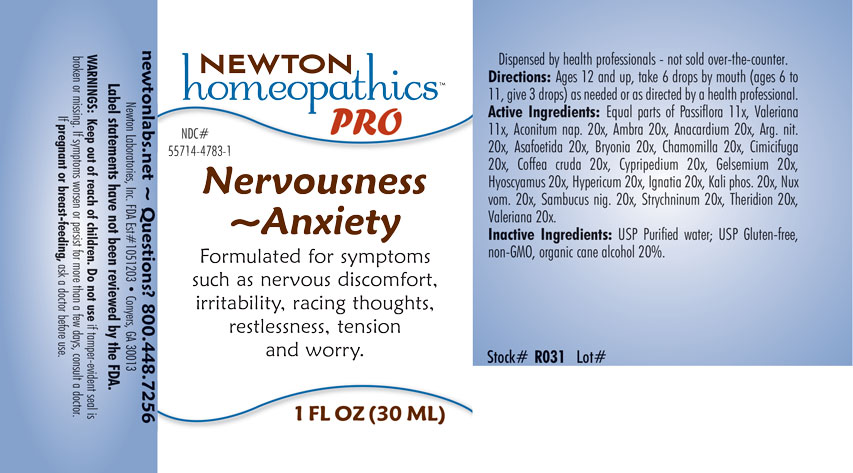 DRUG LABEL: Nervousness - Anxiety
NDC: 55714-4783 | Form: LIQUID
Manufacturer: Newton Laboratories, Inc.
Category: homeopathic | Type: HUMAN OTC DRUG LABEL
Date: 20201204

ACTIVE INGREDIENTS: ACONITUM NAPELLUS 20 [hp_X]/1 mL; AMBERGRIS 20 [hp_X]/1 mL; SEMECARPUS ANACARDIUM JUICE 20 [hp_X]/1 mL; SILVER NITRATE 20 [hp_X]/1 mL; FERULA ASSA-FOETIDA RESIN 20 [hp_X]/1 mL; BRYONIA ALBA ROOT 20 [hp_X]/1 mL; MATRICARIA CHAMOMILLA 20 [hp_X]/1 mL; BLACK COHOSH 20 [hp_X]/1 mL; ARABICA COFFEE BEAN 20 [hp_X]/1 mL; CYPRIPEDIUM PARVIFLORUM VAR. PUBESCENS ROOT 20 [hp_X]/1 mL; GELSEMIUM SEMPERVIRENS ROOT 20 [hp_X]/1 mL; HYOSCYAMUS NIGER 20 [hp_X]/1 mL; HYPERICUM PERFORATUM 20 [hp_X]/1 mL; STRYCHNOS IGNATII SEED 20 [hp_X]/1 mL; DIBASIC POTASSIUM PHOSPHATE 20 [hp_X]/1 mL; STRYCHNOS NUX-VOMICA SEED 20 [hp_X]/1 mL; SAMBUCUS NIGRA FLOWERING TOP 20 [hp_X]/1 mL; STRYCHNINE 20 [hp_X]/1 mL; THERIDION CURASSAVICUM 20 [hp_X]/1 mL; VALERIAN 20 [hp_X]/1 mL; PASSIFLORA INCARNATA FLOWERING TOP 11 [hp_X]/1 mL
INACTIVE INGREDIENTS: WATER; ALCOHOL

Nervousness 4783L

INDICATIONS & USAGE SECTION

Formulated for symptoms such as nervous discomfort, irritability, racing thoughts, restlessness, tension and worry.

DOSAGE & ADMINISTRATION SECTION

Directions: Ages 12 and up, take 6 drops by moouth (ages 0 to 11, give 3 drops) as needed or as directed by a health professional.

OTC - ACTIVE INGREDIENT SECTION

Equal parts of Passiflora incarnata 11x, Valeriana officinalis 11x, Aconitum napellus 20x, Ambra grisea 20x, Anacardium orientale 20x, Argentum nitricum 20x, Asafoetida 20x, Bryonia 20x, Chamomilla 20x, Cimicifuga racemosa 20x, Coffea cruda 20x, Cypripedium pubescens 20x, Gelsemium sempervirens 20x, Hyoscyamus niger 20x, Hypericum perforatum 20x, Ignatia amara 20x, Kali phosphoricum 20x, Nux vomica 20x, Sambucus nigra 20x, Strychninum 20x, Theridion 20x, Valeriana officinalis 20x.

OTC - PURPOSE SECTION

Formulated for symptoms such as nervous discomfort, irritability, racing thoughts, restlessness, tension and worry.

INACTIVE INGREDIENT SECTION

Inactive Ingredients: USP Purified Water; USP Gluten-free, non-GMO, organic cane alcohol 20%.

QUESTIONS SECTION

newtonlabs.net – Questions? 800.448.7256

Newton Laboratories, Inc. FDA Est # 1051203 - Conyers, GA 30013

WARNINGS SECTION

WARNINGS: Keep out of reach of children. Do not use if tamper-evident seal is broken or missing. If symptoms worsen or persist for more than a few days, consult a doctor. If pregnant or breast-feeding, ask a doctor before use.

OTC - PREGNANCY OR BREAST FEEDING SECTION

If pregnant or breast-feeding, ask a doctor before use.

OTC - KEEP OUT OF REACH OF CHILDREN SECTION

Keep out of reach of children.